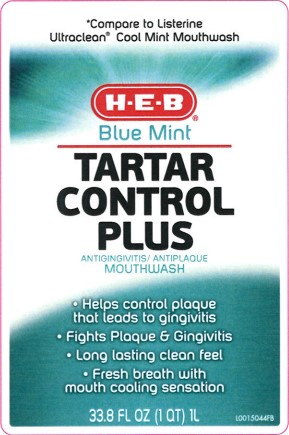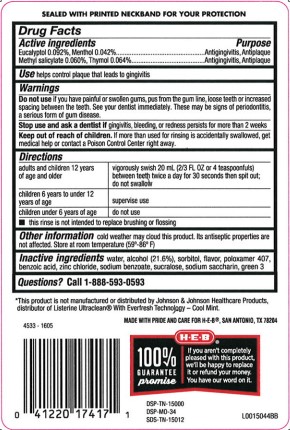 DRUG LABEL: Tartar control plus
NDC: 37808-855 | Form: MOUTHWASH
Manufacturer: H E B
Category: otc | Type: HUMAN OTC DRUG LABEL
Date: 20260224

ACTIVE INGREDIENTS: EUCALYPTOL 0.92 mg/1 mL; MENTHOL 0.42 mg/1 mL; METHYL SALICYLATE 0.6 mg/1 mL; THYMOL 0.64 mg/1 mL
INACTIVE INGREDIENTS: ALCOHOL; WATER; SORBITOL; POLOXAMER 407; BENZOIC ACID; ZINC CHLORIDE; SODIUM BENZOATE; SUCRALOSE; SACCHARIN SODIUM; FD&C GREEN NO. 3

HEB 855.000/855AA-AC
Tartar Control Plus Antiseptic Mouth Rinse, Blue Mint

Tamper Evident Statement

SEALED WITH PRINTED NECKBAND FOR YOUR PROTECTION

Active ingredients

Eucalyptol 0.092%

Menthol 0.042%

Methyl salicylate 0.060%

Thymol 0.064%

Purpose

Antigingivitis, antiplaque

Use

helps control plaque that leads to gingivitis

Warnings

For this product

Do not use

if you have painful or swollen gums, pus from the gum line, loose teeth or increased spacing between the teeth. See your dentist immediately. These may be signs of periodontitis, a serious form of gum disease.

Stop use and ask a dentist if

gingivitis, bleeding, or redness persists for more than 2 weeks.

Keep out of reach of children.

If more than used for rinsing is accidentally swallowed, get medical help or contact a Poison Control Center right away.

Directions

adults and children 12 years of age and older - vigorously swish 20 mL (2/3 FL OZ or 4 teaspoonfuls) between teeth twice a day for 30 seconds then spit out; do not swallow

children 6 years to under 12 years of age - supervise use

children under 6 years of age - do not use

- this rinse is not intended to replace brushing or flossing

Other information

cold weather may cloud this product. Its antiseptic properties are not affected. Store at room temperature (59°-86°F)

Inactive ingredients

water, alcohol 21.6%, sorbitol, flavor, poloxamer 407, benzoic acid, zinc chloride, sodium benzoate, sucralose, sodium saccharin, green 3

Questions?

1-888-593-0593

Disclaimer

*This product is not manufactured or distributed by Johnson & Johnson Healthcare Products, distributor of Listerine UltracleanWith Everfresh Technology - Cool Mint.

Adverse Reactions

MADE WITH PRIDE AND CARE FOR H-E-B, SAN ANTONIO, TN 78204

100% GUARANTEE PROMISE

If you aren't completely pleased with the product, we'll be happy to replace it or refund your money.

You have our word on it.

DSP-TN-15000

DSP-MO-34

SDS-TN-15012

principal display panel

*Compare to Listerine Ultraclean®Cool Mint Mouthwash

H-E-B®

Blue Mint

TARTAR

CONTROL

PLUS

ANTIGINGIVITIS/ANTIPLAQUE

MOUTHWASH

- Helps control plaque that leads to gingivitis
- Fights Plaque & Gingivitis
- Long lasting clean feel
- Fresh breath with mouth cooling sensation

33.8 FL OZ (1 QT) 1 L